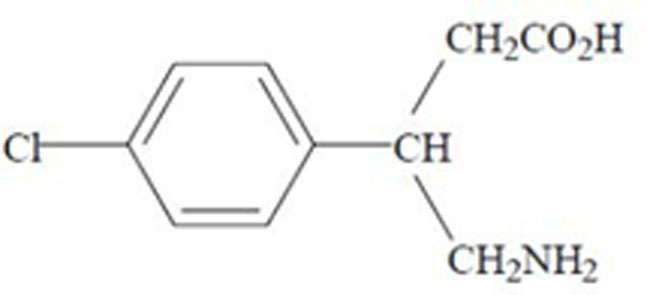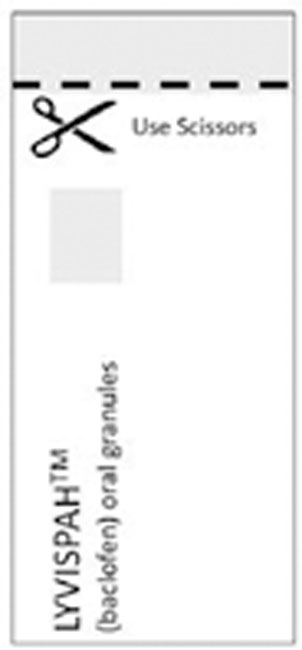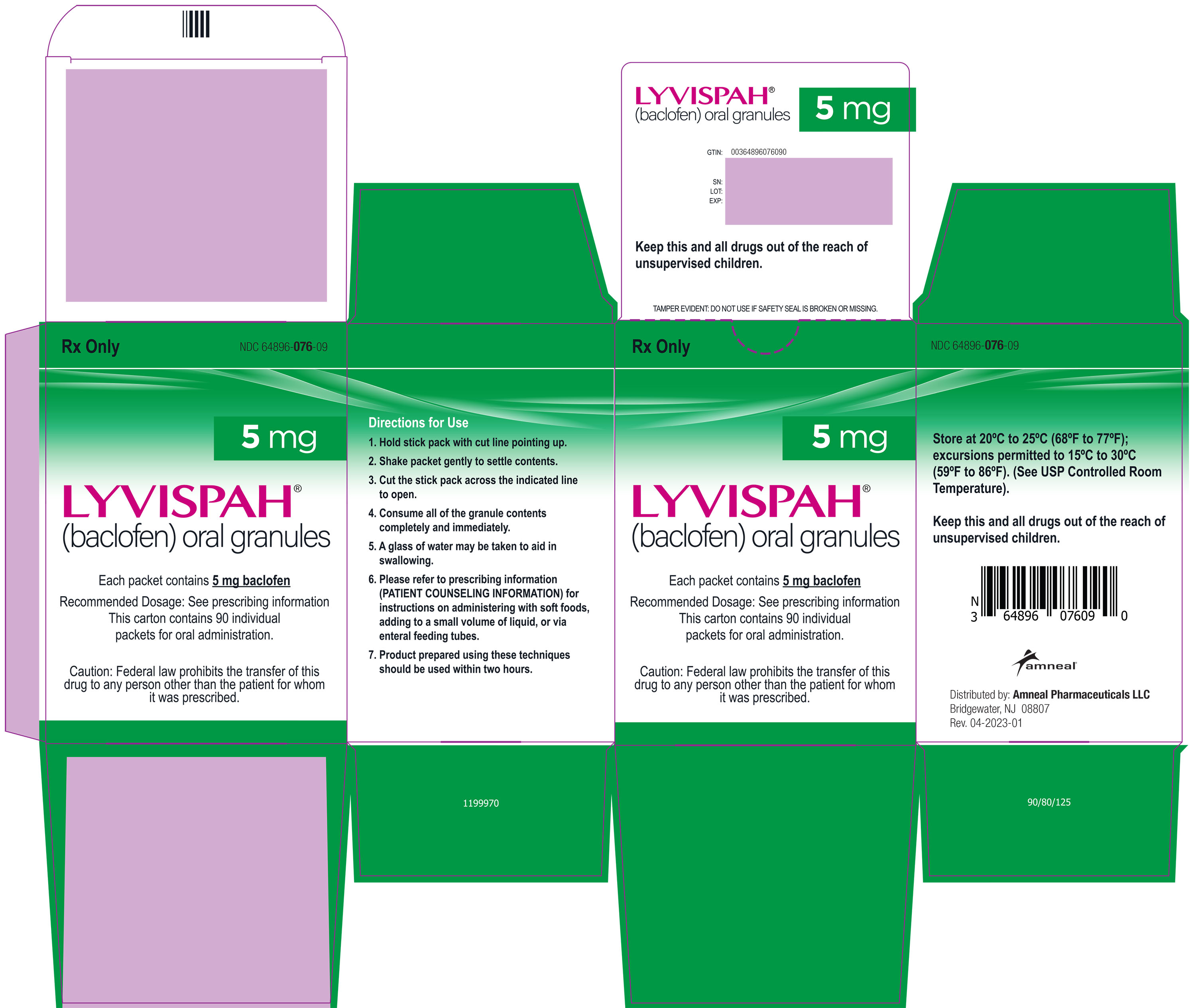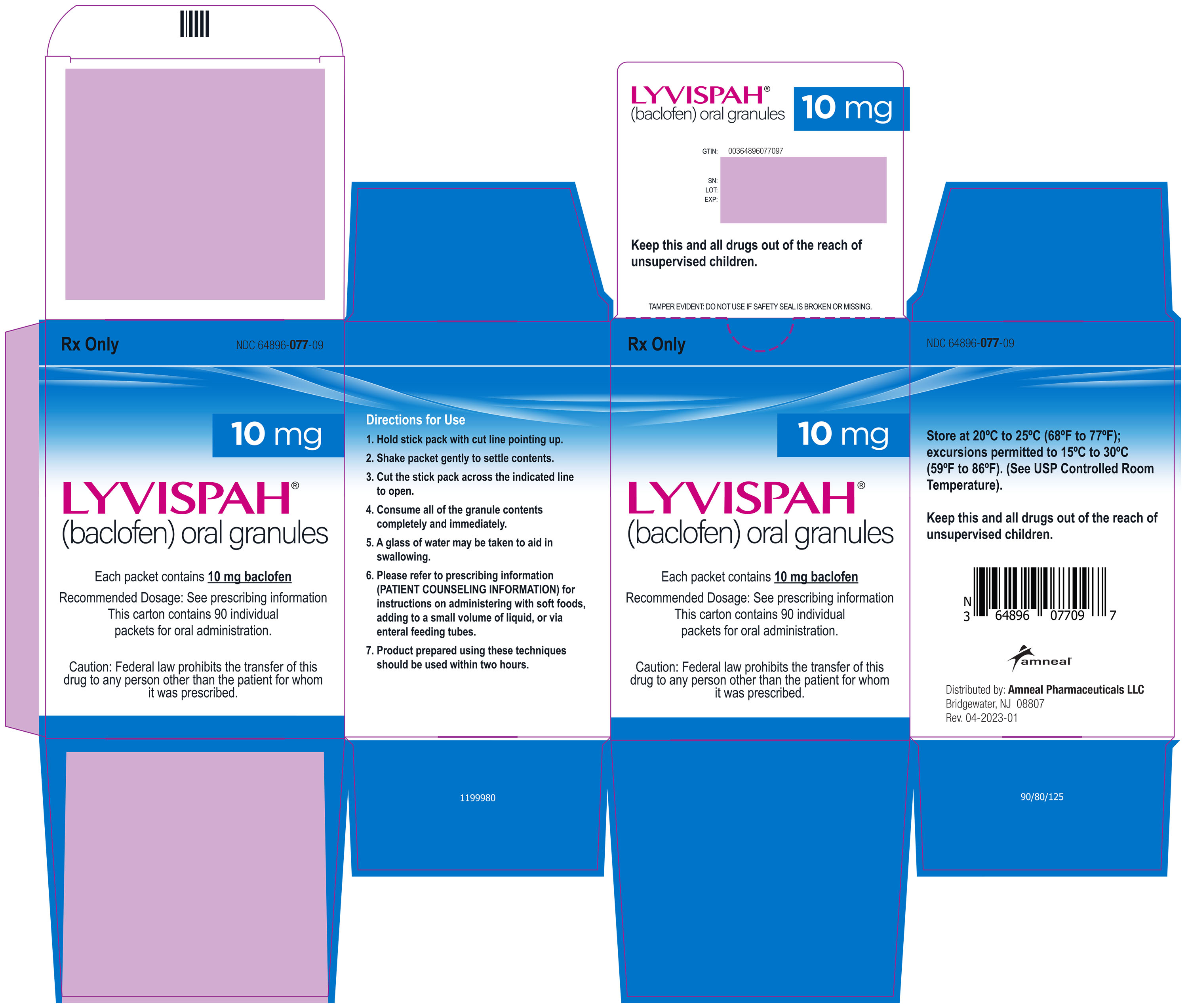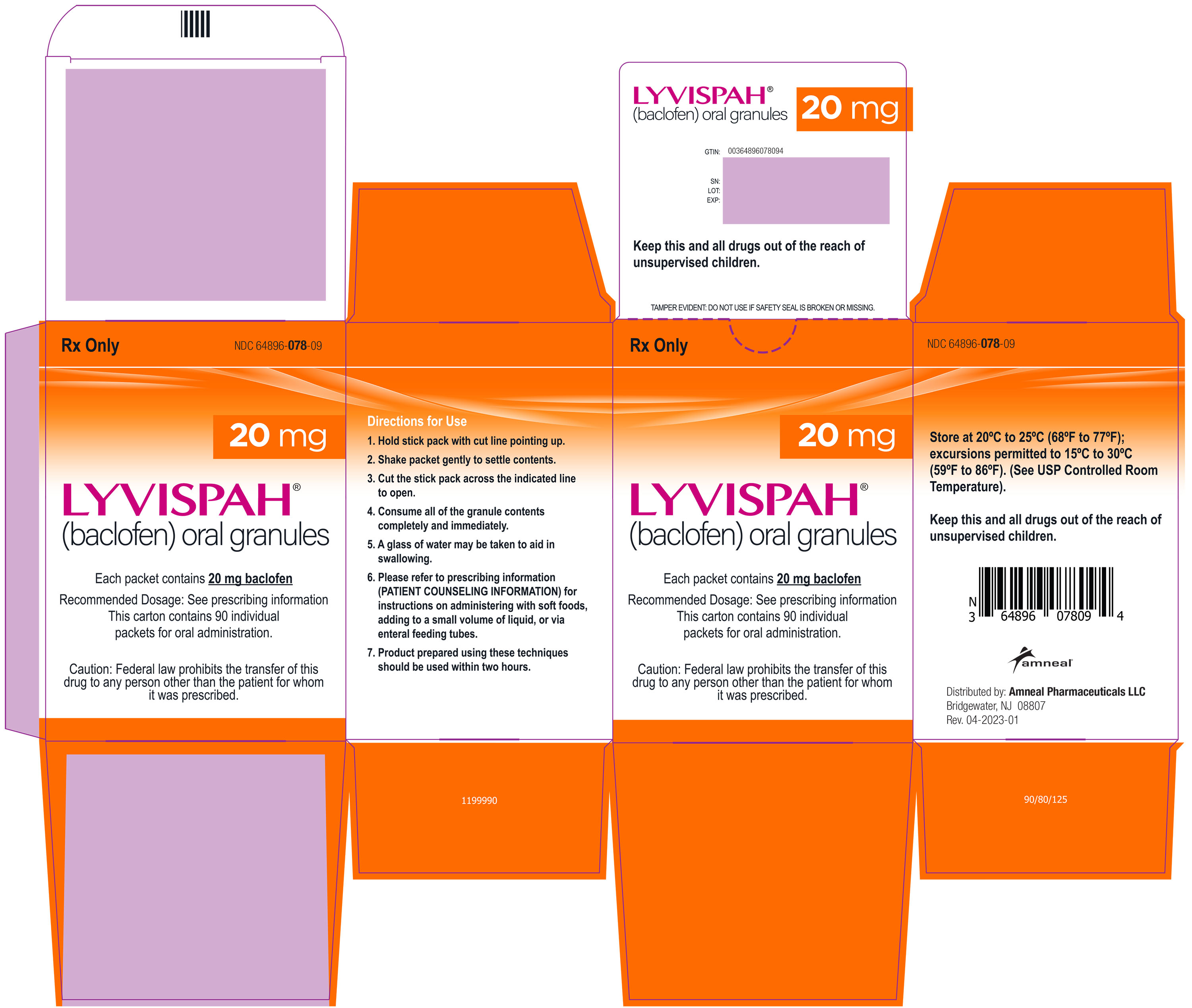 DRUG LABEL: LYVISPAH
NDC: 64896-076 | Form: GRANULE
Manufacturer: Amneal Pharmaceuticals LLC
Category: prescription | Type: HUMAN PRESCRIPTION DRUG LABEL
Date: 20230423

ACTIVE INGREDIENTS: BACLOFEN 5 mg/1 1
INACTIVE INGREDIENTS: DIMETHYLAMINOETHYL METHACRYLATE - BUTYL METHACRYLATE - METHYL METHACRYLATE COPOLYMER; CALCIUM STEARATE; SILICON DIOXIDE; CROSPOVIDONE; HYPROMELLOSES; MANNITOL; SACCHARIN SODIUM; TALC; XYLITOL

HIGHLIGHTS OF PRESCRIBING INFORMATION

These highlights do not include all the information needed to use LYVISPAH safely and effectively. See full prescribing information for LYVISPAH.
LYVISPAH (baclofen) oral granules
Initial U.S. Approval: 1977

1 INDICATIONS AND USAGE

- LYVISPAH is a gamma-aminobutyric acid (GABA-ergic) agonist indicated for the treatment of spasticity resulting from multiple sclerosis, particularly for the relief of flexor spasms and concomitant pain, clonus, and muscular rigidity. (1)
- LYVISPAH may also be of some value in patient with spinal cord injuries and other spinal cord diseases. (1)

Limitations of Use

LYVISPAH is not indicated in the treatment of skeletal muscle spasm resulting from rheumatic disorders. (1)

2 DOSAGE AND ADMINISTRATION

- Initiate LYVISPAH with a low dosage, preferably in divided doses, administered orally. Increase gradually based on clinical response and tolerability. (2.1)
- The maximum dosage is 80 mg daily (20 mg four times a day). (2.1)
- LYVISPAH can be taken with or without water. (2.2)
- LYVISPAH oral granules can be mixed with soft food for administration within 2 hours. (2.2)
- LYVISPAH oral granules can be administered via enteral feeding tubes. (2.2)
- When discontinuing, reduce the dose slowly. (2.2)

3 DOSAGE FORMS AND STRENGTHS

Oral granules: 5 mg, 10 mg, or 20 mg baclofen in a packet (3)

4 CONTRAINDICATIONS

- Hypersensitivity to baclofen (4)

5 WARNINGS AND PRECAUTIONS

- Abrupt discontinuation of baclofen has resulted in serious adverse reactions including death; therefore, reduce the dosage slowly when LYVISPAH is discontinued. (5.1)
- Neonatal withdrawal symptoms can occur; gradually reduce the dosage and discontinue LYVISPAH before delivery. (5.2)
- LYVISPAH can cause drowsiness and sedation. Patients should avoid the operation of automobiles or other dangerous machinery until they know how the drug affects them. Advise patients that the central nervous system effects of LYVISPAH may be additive to those of alcohol and other CNS depressants. (5.3)
- LYVISPAH can cause exacerbation of the following: psychotic disorders, schizophrenia, or confusional states; autonomic dysreflexia; epilepsy. Use with caution in patients with these conditions. (5.5, 5.6, 5.7)

6 ADVERSE REACTIONS

The most common adverse reactions (up to 15% or more) in patients were drowsiness, dizziness, and weakness. (6.1)

To report SUSPECTED ADVERSE REACTIONS, contact Amneal Pharmaceuticals at 1-877-835-5472 or FDA at 1-800-FDA-1088 or www.fda.gov/medwatch.

8 USE IN SPECIFIC POPULATIONS

- Pregnancy: Based on animal data, may cause fetal harm (8.1)
- Because baclofen is excreted unchanged through the kidneys it may be necessary to reduce the dosage in patients with impaired renal function. (8.6)

FULL PRESCRIBING INFORMATION

1 INDICATIONS AND USAGE

LYVISPAH is indicated for the treatment of spasticity resulting from multiple sclerosis, particularly for the relief of flexor spasms and concomitant pain, clonus, and muscular rigidity.

LYVISPAH may also be of some value in patients with spinal cord injuries and other spinal cord diseases.

Limitations of Use

LYVISPAH is not indicated in the treatment of skeletal muscle spasm resulting from rheumatic disorders.

2 DOSAGE AND ADMINISTRATION

2.1 Recommended Dosage

Initiate LYVISPAH with a low dosage, preferably in divided doses, administered orally. The following gradually increasing dosage regimen is suggested, but should be adjusted based on clinical response and tolerability:

5 mg three times a day for three days 10 mg three times a day for three days 15 mg three times a day for three days 20 mg three times a day for three days

Additional increases may be necessary up to the maximum recommended dosage of 80 mg daily (20 mg four times a day). Multiple packets or multiple strengths can be used to achieve the prescribed dosage.

2.2 Administration Instructions

The entire contents of the packet should be emptied into the mouth. The granules will dissolve in the mouth or can be swallowed. LYVISPAH can be taken with liquids or soft foods if needed.

Administration with Liquids or Soft Foods

LYVISPAH can be administered orally as a mixture with liquids or soft foods, such as apple sauce, yogurt, or pudding. The contents of one packet can be emptied and mixed with up to 15 mL of liquid or soft food. The mixture should be administered no more than 2 hours after mixing. If multiple packets are to be administered, each packet must be mixed with a separate volume of liquid or soft food.

Administration via Feeding Tube

LYVISPAH can also be administered via enteral feeding tubes such as nasogastric (NG) at sizes 8 FR or higher, gastrostomy (G) at sizes 12 FR or higher, percutaneous endoscopic gastrostomy (PEG) at sizes 14 FR or higher, and gastrojejunostomy (GJ) tubes at sizes 16 FR or higher.

- Flush the feeding tube with up to 15 mL of water using a catheter tip syringe.
- Open and empty the full contents of one packet of LYVISPAH in 15 mL of liquid, such as apple juice or milk, in a clean container. Mix the suspension to ensure all granules are wetted.
- Draw up the suspension of granules into a dosing syringe immediately after mixing and administer the dose via the feeding tube. Administration should be no longer than two hours after mixing. If the syringe is allowed to stand for 15 minutes before administration, invert the syringe three times.
- Refill the dosing syringe with 15 mL of water and flush the feeding tube.
- If multiple packets are to be administered, each packet must be mixed with a separate volume of liquid.

2.3 Discontinuation of LYVISPAH

When discontinuing LYVISPAH, reduce the dosage slowly and avoid abrupt withdrawal from the drug to help minimize the risk of adverse reactions [see Warnings and Precautions (5.1)].

3 DOSAGE FORMS AND STRENGTHS

Oral Granules: 5 mg, 10 mg, or 20 mg baclofen as white to off-white, strawberry flavored granules in a single dose packet.

4 CONTRAINDICATIONS

LYVISPAH is contraindicated in patients with hypersensitivity to baclofen.

5 WARNINGS AND PRECAUTIONS

5.1 Adverse Reactions from Abrupt Withdrawal of LYVISPAH

Abrupt discontinuation of baclofen, regardless of the cause, has resulted in adverse reactions that include hallucinations, seizures, high fever, altered mental status, exaggerated rebound spasticity, and muscle rigidity, that in rare cases has advanced to rhabdomyolysis, multiple organ-system failure, and death. Therefore, reduce the dosage slowly when LYVISPAH is discontinued, unless the clinical situation justifies a rapid withdrawal.

5.2 Neonatal Withdrawal Symptoms

Withdrawal symptoms in neonates whose mothers were treated with oral baclofen throughout pregnancy have been reported starting hours to days after delivery. The symptoms of withdrawal in these infants have included increased muscle tone, tremor, jitteriness, and seizure. If the potential benefit justifies the potential risk to the fetus and LYVISPAH is continued during pregnancy, gradually reduce the dosage, and discontinue LYVISPAH before delivery. If slow withdrawal is not feasible, advise the parents or caregivers of the exposed neonate of the potential for neonatal withdrawal.

5.3 Drowsiness and Sedation

Drowsiness and sedation have been reported in up to 63% of patients taking baclofen, the active ingredient in LYVISPAH [see Adverse Reactions (6.1)]. Patients should avoid operation of automobiles or other dangerous machinery and activities made hazardous by decreased alertness when starting LYVISPAH or increasing the dosage until they know how the drug affects them. Advise patients that the central nervous system depressant effects of LYVISPAH may be an additive to those of alcohol and other CNS depressants.

5.4 Poor Tolerability in Stroke Patients

LYVISPAH should be used with caution in patients who have had a stroke. Baclofen has not significantly benefited patients with stroke. These patients have also shown poor tolerability to the drug.

5.5 Exacerbation of Psychotic Disorders, Schizophrenia, or Confusional States

LYVISPAH should be used with caution in patients suffering from psychotic disorders, schizophrenia, or confusional states. If treated with LYVISPAH, these patients should be kept under careful surveillance because exacerbations of these conditions have been observed with oral baclofen administration.

5.6 Exacerbation of Autonomic Dysreflexia

LYVISPAH should be used with caution in patients with a history of autonomic dysreflexia. The presence of nociceptive stimuli or abrupt withdrawal of LYVISPAH may cause an autonomic dysreflexic episode.

5.7 Exacerbation of Epilepsy

LYVISPAH should be used with caution in patients with epilepsy. Deterioration in seizure control has been reported in patients taking baclofen.

5.8 Posture and Balance Effects

LYVISPAH should be used with caution in patients where spasticity is utilized to sustain upright posture and balance in locomotion or whenever spasticity is utilized to obtain increased function.

5.9 Ovarian Cysts

A dose-related increase in incidence of ovarian cysts was observed in female rats treated chronically with oral baclofen. Ovarian cysts have been found by palpation in about 4% of the multiple sclerosis patients who were treated with oral baclofen for up to one year. In most cases, these cysts disappeared spontaneously while patients continue to receive the drug. Ovarian cysts are estimated to occur spontaneously in approximately 1% to 5% of the normal female population.

6 ADVERSE REACTIONS

The following clinically significant adverse reactions are described elsewhere in the labeling:

- Adverse Reactions from Abrupt Withdrawal of LYVISPAH [see Warnings and Precautions (5.1)]
- Neonatal Withdrawal Symptoms [see Warnings and Precautions (5.2)]
- Drowsiness and Sedation [see Warnings and Precautions (5.3)]
- Poor Tolerability in Stroke Patients [see Warnings and Precautions (5.4)]
- Exacerbation of Psychotic Disorders, Schizophrenia, or Confusional States [see Warnings and Precautions (5.5)]
- Exacerbation of Autonomic Dysreflexia [see Warnings and Precautions (5.6)]
- Exacerbation of Epilepsy [see Warnings and Precautions (5.7)]
- Posture and Balance Effects [see Warnings and Precautions (5.8)]
- Ovarian Cysts [see Warnings and Precautions (5.9)]

6.1 Clinical Trials Experience

Because clinical trials are conducted under widely varying conditions, adverse reaction rates observed in the clinical trials of a drug cannot be directly compared to rates in the clinical trials of another drug and may not reflect the rates observed in practice.

The most common adverse reaction is transient drowsiness. In one controlled study of 175 patients, transient drowsiness was observed in 63% of those receiving baclofen compared to 36% of those in the placebo group. Other common adverse reactions (up to 15%) are dizziness and weakness.

Adverse reactions with a frequency of ≥1% are listed in Table 1.

Table 1. Common (≥1%) Adverse Reactions in Patients Treated with Baclofen for Spasticity

ADVERSE REACTION | PERCENT
Drowsiness | 10-63%
Dizziness | 5-15%
Weakness | 5-15%
Nausea | 4-12%
Confusion | 1-11%
Hypotension | 0-9%
Headache | 4-8%
Insomnia | 2-7%
Constipation | 2-6%
Urinary Frequency | 2-6%
Fatigue | 2-4%

The following adverse reactions not included in Table 1, classified by body system, were also reported:

Neuropsychiatric: euphoria, excitement, depression, hallucinations, paresthesia, muscle pain, tinnitus, slurred speech, coordination disorder, tremor, rigidity, dystonia, ataxia, blurred vision, nystagmus, strabismus, miosis, mydriasis, diplopia, dysarthria, epileptic seizure Cardiovascular: dyspnea, palpitation, chest pain, syncope

Gastrointestinal: dry mouth, anorexia, taste disorder, abdominal pain, vomiting, diarrhea, and positive test for occult blood in stool

Genitourinary: enuresis, urinary retention, dysuria, impotence, inability to ejaculate, nocturia, hematuria

Other: rash, pruritus, ankle edema, excessive perspiration, weight gain, nasal congestion

The following laboratory tests have been found to be abnormal in patients receiving baclofen: increased SGOT, elevated alkaline phosphatase, and elevation of blood sugar.

7 DRUG INTERACTIONS

7.1 CNS Depressants and Alcohol

LYVISPAH can cause CNS depression, including drowsiness and sedation, which may be an additive when used concomitantly with other CNS depressants or alcohol [see Warnings and Precautions (5.3)].

8 USE IN SPECIFIC POPULATIONS

8.1 Pregnancy

Risk Summary

There are no adequate data on the risk of major birth defects, miscarriages, or other maternal adverse outcomes associated with the use of LYVISPAH in pregnant women. There are adverse effects on fetal outcomes associated with withdrawal from baclofen after delivery (see Clinical Considerations). Oral administration of baclofen to pregnant rats resulted in an increased incidence of fetal structural abnormalities at a dose which was also associated with maternal toxicity. The background risk of major birth defects and miscarriage for the indicated population is unknown. In the U.S. general population, the estimated background risk of major birth defects and miscarriage in clinically recognized pregnancies is 2-4% and 15-20%, respectively.

Clinical Considerations

Fetal/Neonatal Adverse Reactions

LYVISPAH may increase the risk of late-onset neonatal withdrawal symptoms [see Warnings and Precautions (5.2)].

Data

Animal Data

Baclofen given orally has been shown to increase the incidence of omphaloceles (ventral hernias) in fetuses of rats given approximately 13 times on a mg/kg basis, or 3 times on a mg/m² basis, the maximum oral dose recommended for human use; this dose also caused reductions in food intake and weight gain in the dams. This abnormality was not seen in mice or rabbits.

8.2 Lactation

Risk Summary

At recommended oral doses, baclofen is present in human milk. There are no human data on effects of baclofen on milk production. Withdrawal symptoms can occur in breastfed infants when maternal administration of LYVISPAH is stopped, or when breastfeeding is stopped [see Warnings and Precautions (5.2)]. There are no adequate data on other effects of baclofen on the breastfed infant.

The developmental and health benefits of breastfeeding should be considered along with the mother’s clinical need for LYVISPAH and any potential adverse effects on the breastfed infant from LYVISPAH or from the underlying maternal condition.

8.4 Pediatric Use

Safety and effectiveness in pediatric patients below the age of 12 have not been established.

8.5 Geriatric Use

In general, dose selection for an elderly patient should be cautious, usually starting at the low end of the dosing range, reflecting the greater frequency of decreased hepatic, renal, or cardiac function, and of concomitant disease or other drug therapy. This drug is known to be substantially excreted by the kidney, and the risk of adverse reactions to this drug may be greater in patients with impaired renal function. Because elderly patients are more likely to have decreased renal function, care should be taken in dose selection, and it may be useful to monitor renal function [see Use in Specific Populations (8.6)].

8.6 Renal Impairment

Because baclofen is primarily excreted unchanged through the kidneys, LYVISPAH should be given with caution to patients with renal impairment, and it may be necessary to reduce the dosage.

10 OVERDOSAGE

10.1 Symptoms of Baclofen Overdose

With overdose of baclofen, patients may present in coma or with progressive drowsiness, lightheadedness, dizziness, somnolence, accommodation disorders, respiratory depression, seizures, or hypotonia progressing to loss of consciousness.

10.2 Treatment for Overdose

The treatment of baclofen overdose includes gastric decontamination, maintaining an adequate airway and respirations.

11 DESCRIPTION

LYVISPAH (baclofen) oral granules is a gamma-aminobutyric acid (GABA-ergic) agonist available as 5 mg, 10 mg, or 20 mg of baclofen oral granules in a packet. Its chemical name is 4-amino-3-(4- chlorophenyl)-butanoic acid and its structural formula is:

Molecular formula is C10H12ClNO2 Molecular Weight is 213.66.

Baclofen USP is a white to off-white, odorless or practically odorless crystalline powder. It is slightly soluble in water, very slightly soluble in methanol, and insoluble in chloroform.

LYVISPAH (baclofen) oral granules inactive ingredients include amino methacrylate copolymer, calcium stearate, colloidal silicon dioxide, crospovidone, hypromellose, mannitol, saccharin sodium, strawberry flavor, talc, and xylitol.

12 CLINICAL PHARMACOLOGY

12.1 Mechanism of Action

The precise mechanism of action of baclofen is not fully understood. Baclofen inhibits both monosynaptic and polysynaptic reflexes at the spinal level, possibly by decreasing excitatory neurotransmitter release from afferent terminals, although actions at supraspinal sites may also occur and contribute to its clinical effect. Baclofen is a structural analog of the inhibitory neurotransmitter gamma-aminobutyric acid (GABA), and may exert its effects by stimulation of the GABA-B receptor subtype.

12.2 Pharmacodynamics

Baclofen has been shown to have general CNS depressant properties, as indicated by the production of sedation with tolerance, somnolence, ataxia, and respiratory and cardiovascular depression [see Warnings and Precautions (5.3), Adverse Reactions (6.1), and Overdosage (10.1)].

12.3 Pharmacokinetics

Pharmacokinetic studies in heathy adult subjects under fasting conditions at 20 mg dose level demonstrated similar bioavailability for baclofen oral granules and oral tablets.

Absorption

The peak plasma concentrations of baclofen oral granule formulation were achieved in about one hour and the apparent elimination half-life is about 5.5 hours. The exposure of baclofen was dose proportional across the dose range of 5 mg, 10 mg, and 20 mg.

Effect of Food

Administering LYVISPAH with or without water, or with applesauce did not affect the bioavailability of baclofen oral granules. Administration with a high fat meal resulted in 10% decrease in AUC and 29% decrease in Cmax compared to the fasted state.

Elimination

Baclofen is excreted primarily by the kidney in unchanged form, and there is relatively large intersubject variation in absorption and/or elimination.

13 NONCLINICAL TOXICOLOGY

13.1 Carcinogenesis and Mutagenesis and Impairment of Fertility

Carcinogenesis

No increase in tumors was seen in rats receiving baclofen orally for two years at approximately 30 to 60 times on a mg/kg basis, or 10 to 20 times on a mg/m2 basis, the maximum oral dose recommended for human use.

Mutagenesis

Genetic toxicology assays have not been conducted for baclofen.

Impairment of Fertility

Studies to evaluate the effects of baclofen on fertility have not been conducted.

14 CLINICAL STUDIES

The efficacy of LYVISPAH is based upon a bioavailability study in healthy adults comparing baclofen oral tablets to LYVISPAH [see Clinical Pharmacology (12.3)].

16 HOW SUPPLIED

16.1 How Supplied

LYVISPAH (baclofen) oral granules is supplied as follows:

- 5 mg white to off-white, strawberry flavored oral granules in a child-resistant single dose packet
  - NDC 64896-076-09: carton of 90 packets
- 10 mg white to off-white, strawberry flavored oral granules in a child-resistant single dose packet
  - NDC 64896-077-09: carton of 90 packets
- 20 mg white to off-white, strawberry flavored oral granules in a child-resistant single dose packet
  - NDC 64896-078-09: carton of 90 packets

16.2 Storage and Handling

Store at room temperature, 20ºC to 25ºC (68ºF to 77ºF); excursions permitted between 15ºC to 30º C (59ºF to 86ºF) [see USP Controlled Room Temperature].

17 PATIENT COUNSELING INFORMATION

Advise the patient or caregiver to read the FDA-approved patient labeling (Patient Information and Instructions for Use).

General Administration Instructions

Instruct patient or caregiver to carefully open the LYVISPAH packet and empty the entire contents, to obtain the prescribed amount of medication. Packet contents can be administered directly into the mouth. The contents of the packet can be swallowed or will dissolve in the mouth. LYVISPAH may be taken with liquids or can also be administered in soft foods if needed [see Dosage and Administration (2.2)].

Administration Instructions with Soft Foods

LYVISPAH can also be administered by mouth as a mixture with liquids or soft foods, such as apple sauce, yogurt, or pudding. One packet can be mixed with up to 15 mL (one tablespoonful) of soft food. The mixture should be administered no more than 2 hours after mixing [see Dosage and Administration (2.2)].

Administration Instructions via Feeding Tubes

LYVISPAH can be administered via enteral feeding tubes, such a nasogastric (NG), gastrostomy (G), percutaneous endoscopic gastrostomy (PEG), and gastrojejunostomy (GJ) tubes.

- Flush the feeding tube with up to 15 mL (one tablespoonful) of water.
- Open and empty the full contents of one packet of LYVISPAH in 15 mL (one tablespoonful) of the preferred liquid. Stir the suspension to ensure all granules are wetted.
- Draw up the suspension of granules into a dosing syringe immediately after stirring and administer the dose via the feeding tube. Administer no longer than two hours after mixing.
- Refill the dosing syringe with 15 mL (one tablespoonful) of water and flush the feeding tube with the remaining contents.
- Any unused suspensions should be discarded.

Risks Related to Sudden Withdrawal of LYVISPAH

Advise patients and caregivers not to discontinue use of LYVISPAH without consulting with their healthcare provider because sudden withdrawal of LYVISPAH can result in serious complications that include hallucinations, seizures, high fever, confusion, muscle stiffness, multiple organ-system failure, and death [see Warnings and Precautions (5.1)]. Inform patients that early symptoms of LYVISPAH withdrawal may include increased spasticity, itching, and tingling of extremities.

Neonatal Withdrawal Symptoms

Advise patients to notify their healthcare provider if they are pregnant, plan to become pregnant, or plan to breastfeed [see Warnings and Precautions (5.2) and Use in Specific Populations (8.2)].

Increased Risk of Drowsiness with Alcohol and Other CNS Depressants

Advise patients that LYVISPAH may cause drowsiness, and that they should avoid the operation of automobiles or other dangerous machinery, or activities made hazardous by decreased alertness when starting LYVISPAH or increasing the dose of LYVISPAH until they know how the drug affects them [see Warnings and Precautions (5.3)]. Inform patients and their caregivers that the drowsiness associated with LYVISPAH use can be worsened by alcohol and other CNS depressants. Advise patients to read all medicine labels carefully, and to tell their healthcare provider about all prescription and nonprescription drugs they may use.

Distributed by:

Amneal Pharmaceuticals LLC

Bridgewater, NJ 08807

Rev. 04-2023-01

PATIENT INFORMATION

LYVISPAH (lye vis' pah) (baclofen)

oral granules

What is LYVISPAH?

- LYVISPAH is a prescription medicine used to treat muscle stiffness, spasms, and pain from multiple sclerosis.
- LYVISPAH may be used to treat people with spinal cord injuries and other spinal cord diseases.
- LYVISPAH should not be used to treat muscle spasms from inflammatory (rheumatic) disorders.
- It is not known if LYVISPAH is safe and effective in children under 12 years of age.

Do not take LYVISPAH if you:

- are allergic to baclofen. See the end of this Patient Information leaflet for a complete list of ingredients in LYVISPAH.

Before taking LYVISPAH, tell your healthcare provider about all of your medical conditions,

including if you:

- take certain medicines that cause drowsiness.
- have had a stroke.
- are being treated for mental illness, especially a psychotic disorder, schizophrenia, or other illness that may cause you to become confused.
- have or have had high blood pressure.
- have or have had seizures.
- have kidney problems.
- have problems with posture and balance.
- have a history of ovarian cysts
- drink alcohol.
- are pregnant or plan to become pregnant. It is not known if LYVISPAH will harm your unborn baby.
- are breastfeeding or plan to breastfeed. LYVISPAH can pass into your breast milk and may harm your baby. Talk to your healthcare provider about the best way to feed your baby if you take LYVISPAH.

Tell your healthcare provider about all the medicines you take, including prescription and over-the- counter medicines, vitamins, and herbal supplements.

How should I take LYVISPAH?

See the “Instructions for Use” at the end of this Patient Information leaflet for instructions on how to take or give LYVISPAH.

- Take LYVISPAH exactly as your healthcare provider tells you to.
  - Your healthcare provider will start you on a low dose of LYVISPAH and slowly increase your dose as needed.
- LYVISPAH can be taken the following different ways:
  - LYVISPAH granules can be emptied into the mouth. You can let the granules dissolve in your mouth or you can swallow them. LYVISPAH can be taken with or without liquids or with soft foods.
  - LYVISPAH granules from a packet can be mixed with a tablespoonful of liquid or soft foods like apple sauce, yogurt, or pudding. Take LYVISPAH within 2 hours of mixing.
  - LYVISPAH can be given through feeding tubes. See the Instructions for Use for more information.

- Do not stop taking LYVISPAH without talking to your healthcare provider first. Stopping LYVISPAH suddenly can cause serious problems such as severe muscle spasms, organ failure, and death. See “What are the possible side effects of LYVISPAH?”.

What should I avoid while taking LYVISPAH?

- Do not drive, operate dangerous machinery, or do any other dangerous activities until you know how LYVISPAH affects you. LYVISPAH can make you drowsy and less alert when you first start taking LYVISPAH and when your LYVISPAH dose is increased.

What are the possible side effects of LYVISPAH?

LYVISPAH can cause serious side effects, including:

- risk of symptoms from stopping LYVISPAH. Stopping LYVISPAH suddenly can cause severe muscle problems, organ failure, and death. Early symptoms include increased muscle stiffness, itching, and tingling in hands and feet. Other symptoms include seeing or hearing things that are not there (hallucinations), seizures, high fever, and confusion (altered mental status). Your healthcare provider will slowly reduce your dose of LYVISPAH when stopping treatment.
- withdrawal symptoms in infants (Neonatal Withdrawal Symptoms). LYVISPAH can cause withdrawal symptoms in infants after delivery. Symptoms of withdrawal of LYVISPAH in infants include stiffness in arms or legs, tremor, jitteriness, and seizure.
- drowsiness and sedation. If you take certain medicines or drink alcohol while taking LYVISPAH, your drowsiness may get worse. See “What should I avoid while taking LYVISPAH?” and “Before taking LYVISPAH, tell your healthcare provider about all of your medical conditions, including if you:”.
- decreased effectiveness. People who have had a stroke may not respond to or tolerate baclofen, the active ingredient in LYVISPAH.
- increase in symptoms of mental illness especially in people with psychotic disorders, schizophrenia, or other illness that may cause you to become confused.

- sudden increase in high blood pressure (autonomic dysreflexia).

- decrease in seizure control. People who have seizures (epilepsy) may have seizures more often than normal.
- changes in posture and balance. People who take LYVISPAH may have more problems standing or sitting up straight (posture) and keeping their balance.
- fluid filled sac on ovary (ovarian cysts). People may be at increased risk of developing ovarian cysts while taking LYVISPAH.

The most common side effects of LYVISPAH include drowsiness, dizziness, and weakness.

These are not all the side effects of LYVISPAH. Call your doctor for medical advice about side effects. You may report side effects to the FDA at 1-800-FDA-1088 or Amneal Pharmaceuticals at 1-877-835-5472.

How should I store LYVISPAH?

Store LYVISPAH at room temperature between 68°F to 77°F (20°C to 25°C).

General information about the safe and effective use of LYVISPAH.

Medicines are sometimes prescribed for purposes other than those listed in a Patient Information leaflet. Do not use LYVISPAH for a condition for which it was not prescribed. Do not give LYVISPAH to other people, even if they have the same symptoms that you have. It may harm them. You can ask your pharmacist or healthcare provider for information about LYVISPAH that is written for health professionals.

What are the ingredients in LYVISPAH?

Active ingredient: baclofen

Inactive ingredients: amino methacrylate copolymer, calcium stearate, colloidal silicon dioxide, crospovidone, hypromellose, mannitol, saccharin sodium, strawberry flavor, talc, and xylitol.

For more information visit www.lyvispah.comor contact Amneal Pharmaceuticals at 1-877-835-5472

This Patient Information has been approved by the U.S. Food and Drug Administration

Distributed by:

Amneal Pharmaceuticals LLC

Bridgewater, NJ 08807

Rev. 04-2023-01

INSTRUCTIONS FOR USE

LYVISPAH (lye vis' pah) (baclofen)

oral granules

Important information to know before taking LYVISPAH

LYVISPAH can be taken without liquids.

If needed, LYVISPAH can be mixed with liquids or soft foods. LYVISPAH should be taken within 2 hours of mixing into liquids or soft foods.

How to take LYVISPAH? Opening LYVISPAH

Shake the packet to distribute settled granules to the bottom of the packet. Carefully open the LYVISPAH packet by cutting the dotted lines across the top of the packet (see the figure).

Taking LYVISPAH by emptying the granules into the mouth

Empty all the granules in the LYVISPAH packet directly into your mouth. The granules will dissolve in your mouth or can be swallowed. After taking LYVISPAH, you can drink water if needed to swallow any granules left in your mouth.

Taking LYVISPAH with liquids or soft foods

LYVISPAH can be taken or given by mouth as a mixture with liquids such as milk or apple juice. LYVISPAH can also be taken or given by mouth as a mixture with soft foods such as apple sauce, yogurt, or pudding.

1. Open 1 packet of LYVISPAH (see the figure above).
2. Empty the full contents of the LYVISPAH packet into 1 tablespoon (15 mL) liquid or soft food and mix it.
3. Take LYVISPAH within 2 hours of mixing into liquids or soft foods.
4. If more than 1 packet of LYVISPAH is needed for your prescribed dose, mix each packet with a separate amount of liquid or soft food.

Giving LYVISPAH through a feeding tube

LYVISPAH can be given through enteral feeding tubes such as nasogastric (NG), gastrostomy (G), percutaneous endoscopic gastrostomy (PEG), and gastrojejunostomy (GJ) tubes.

1. Flush the feeding tube with up to 1 tablespoon (15 mL) of water using a catheter tip syringe.
2. Open and empty the full contents of 1 packet of LYVISPAH into a clean container and mix with 1 tablespoon (15 mL) of liquid (apple juice or milk).
3. Stir the mixture to make sure all the granules are wet.
4. Draw up the mixture of granules into a dosing syringe right away after stirring.
5. Give the dose of LYVISPAH through the feeding tube within 2 hours after mixing. If the mixture is in the dosing syringe for 15 minutes and not given, turn the dosing syringe upside down 3 times before you give the dose.
6. Fill the dosing syringe with 1 tablespoon (15 mL) of water and flush the feeding tube.
7. If more than 1 packet of LYVISPAH is needed for the prescribed dose, mix each packet with a separate amount of liquid.
8. Throw away (dispose of) any unused mixture.

Important Information

Take the entire packet of LYVISPAH to get the prescribed dose. Do not take only part of the medicine. Do not save a portion for later.

Keep LYVISPAH and all medicines out of the reach of children.

This Patient Information and Instructions for Use have been approved by the US Food and Drug Administration.

Distributed by:

Amneal Pharmaceuticals LLC

Bridgewater, NJ 08807

Rev. 04-2023-01